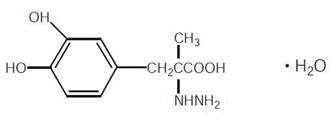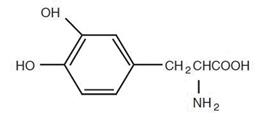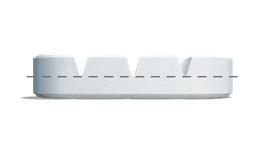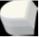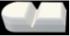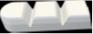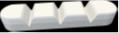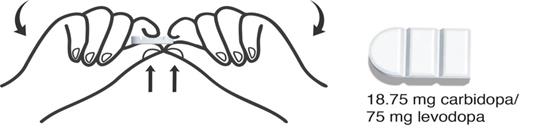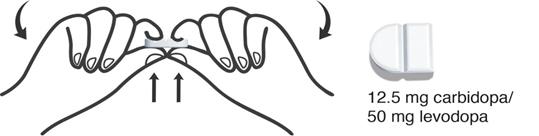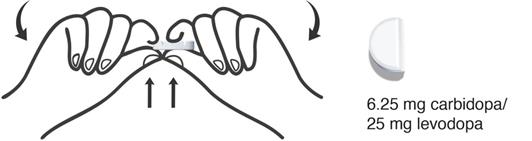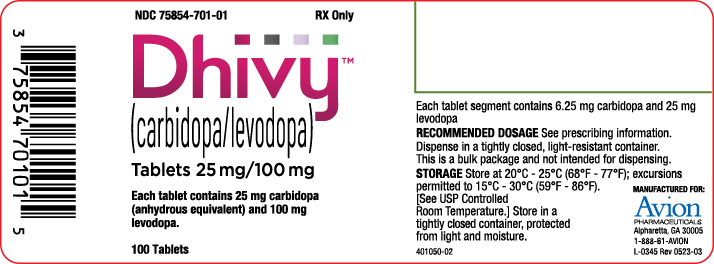 DRUG LABEL: Dhivy
NDC: 75854-701 | Form: TABLET
Manufacturer: Avion Pharmaceuticals, LLC
Category: prescription | Type: HUMAN PRESCRIPTION DRUG LABEL
Date: 20251218

ACTIVE INGREDIENTS: CARBIDOPA 25 mg/1 1; LEVODOPA 100 mg/1 1
INACTIVE INGREDIENTS: MAGNESIUM STEARATE; MICROCRYSTALLINE CELLULOSE; STARCH, CORN

HIGHLIGHTS OF PRESCRIBING INFORMATION

These highlights do not include all the information needed to use DHIVY safely and effectively. See full prescribing information for DHIVY.
DHIVY (carbidopa and levodopa) tablets, for oral use
Initial U.S. Approval: 1975

1 INDICATIONS AND USAGE

DHIVY is a combination of carbidopa (an aromatic amino acid decarboxylation inhibitor) and levodopa (an aromatic amino acid) indicated for the treatment of Parkinson’s disease, post-encephalitic parkinsonism, and symptomatic parkinsonism that may follow carbon monoxide intoxication or manganese intoxication (1)

2 DOSAGE AND ADMINISTRATION

- The recommended starting dosage of DHIVY is one 25 mg /100 mg tablet taken orally three times a day. (2.1)
- Dosage may be increased by up to one whole tablet every day or every other day, as needed, until a maximum dosage of eight whole tablets of DHIVY a day is reached. (2.1)
- Swallow DHIVY with or without food. (2.3)

3 DOSAGE FORMS AND STRENGTHS

Tablets: Carbidopa and levodopa 25 mg/100 mg, functionally scored. Each DHIVY tablet has 3 functional scores with each segment containing 6.25 mg of carbidopa and 25 mg of levodopa.(3)

4 CONTRAINDICATIONS

- Nonselective MAO inhibitors (4)
- With known hypersensitivity to any component of DHIVY (4)

5 WARNINGS AND PRECAUTIONS

- May cause falling asleep during activities of daily living (5.1)
- Avoid sudden discontinuation or rapid dose reduction to reduce the risk of withdrawal-emergent hyperpyrexia and confusion (5.2)
- Cardiovascular Ischemic Events: Monitor patients with a history of cardiovascular disease (5.3)
- Hallucinations/Psychosis may occur (5.4)
- Impulse Control/Compulsive Behaviors: Consider dose reduction or stopping DHIVY if impulse control disorders occur (5.5)
- May cause or exacerbate dyskinesia: Consider dose reduction (5.6)

6 ADVERSE REACTIONS

The most common adverse reactions reported with carbidopa/levodopa tablets have included dyskinesias, such as choreiform, dystonic, and other involuntary movements, and nausea

To report SUSPECTED ADVERSE REACTIONS, contact Avion Pharmaceuticals at 1-888-612-8466 or FDA at 1-800-FDA-1088 or www.fda.gov/medwatch.

7 DRUG INTERACTIONS

Iron salts and dopamine D2 antagonists including metoclopramide: May reduce the effectiveness of DHIVY (7.2, 7.3)

8 USE IN SPECIFIC POPULATIONS

Pregnancy: Based on animal data, may cause fetal harm (8.1)

FULL PRESCRIBING INFORMATION

1 INDICATIONS AND USAGE

DHIVY is indicated for the treatment of Parkinson’s disease, post-encephalitic parkinsonism, and symptomatic parkinsonism that may follow carbon monoxide intoxication or manganese intoxication.

2 DOSAGE AND ADMINISTRATION

2.1 Initial Dosage and Maintenance of Therapy

The recommended starting dosage of DHIVY is one 25 mg / 100 mg tablet taken orally three times a day. This dosage schedule provides 75 mg of carbidopa per day. Dosage may be increased by up to one whole tablet every day or every other day, as needed to a maximum daily dosage of eight whole tablets.

Dosing with DHIVY should be individualized and adjusted according to clinical response and tolerability. The tablet is functionally scored to facilitate dose adjustment. At least 70 mg to 100 mg of carbidopa per day should be provided. Experience with total daily dosages of carbidopa greater than 200 mg is limited.

Monitor patients closely during the dose adjustment period. Specifically, involuntary movements may occur with DHIVY, which may require dosage reduction. Blepharospasm may be a useful early sign of excess dosage in some patients.

Maintain patients on the lowest dosage required to achieve symptomatic control and to minimize adverse reactions, such as dyskinesia and nausea.

2.2 Discontinuation of DHIVY

Avoid sudden discontinuation or rapid dose reduction of DHIVY. The daily dosage of DHIVY should be tapered at the time of treatment discontinuation [see Warnings and Precautions (5.2)].

If general anesthesia is required, DHIVY may be continued as long as the patient is permitted to take fluids and medication by mouth. If therapy is interrupted temporarily, the patient should be observed for symptoms resembling neuroleptic malignant syndrome, and the usual daily dosage may be administered as soon as the patient is able to take oral medication.

2.3 Administration Information

Swallow DHIVY with or without food. The patient should be advised that a change in diet to foods that are high in protein may delay the absorption of levodopa and may reduce the amount taken up in the circulation. Excessive acidity also delays stomach emptying, thus delaying the absorption of levodopa.

If the patient has difficulty swallowing the tablet due to its size, the tablet can be broken at the score lines.

3 DOSAGE FORMS AND STRENGTHS

DHIVY tablets are white to off-white tablets containing 25 mg of carbidopa and 100 mg of levodopa. Each DHIVY tablet has 3 functional scores with each segment containing 6.25 mg of carbidopa and 25 mg of levodopa.

4 CONTRAINDICATIONS

DHIVY is contraindicated in patients

- Currently taking a nonselective monoamine oxidase (MAO) inhibitor (e.g., phenelzine, linezolid, and tranylcypromine) or have recently (within 2 weeks) taken a nonselective MAO inhibitor. Hypertension can occur if these drugs are used concurrently [see Drug Interactions (7.1)] .
- With known hypersensitivity to any component of DHIVY [see Adverse Reactions (6)] .

5 WARNINGS AND PRECAUTIONS

5.1 Falling Asleep During Activities of Daily Living and Somnolence

Patients taking carbidopa/levodopa alone or with other dopaminergic drugs have reported suddenly falling asleep without prior warning of sleepiness while engaged in activities of daily living, including the operation of motor vehicles which have resulted in accidents. Although many patients reported somnolence while on dopaminergic medications, some perceived that they had no warning signs (sleep attack), such as excessive drowsiness, and believed that they were alert immediately prior to the event. Sudden onset of sleep has been reported to occur more than one year after the initiation of treatment.

It has been reported that falling asleep while engaged in activities of daily living usually occurs in a setting of pre-existing somnolence, although some patients may not give such a history. For this reason, prescribers should reassess patients for drowsiness or sleepiness in DHIVY-treated patients, especially since some of the events occur well after the start of treatment. Prescribers should be aware that patients may not acknowledge drowsiness or sleepiness until directly questioned about drowsiness or sleepiness during specific activities.

Before initiating treatment with DHIVY, advise patients about the potential to develop drowsiness and ask specifically about factors that may increase the risk for somnolence with DHIVY such as the use of concomitant sedating medications and the presence of sleep disorders. Consider discontinuing DHIVY in patients who report significant daytime sleepiness or episodes of falling asleep during activities that require active participation (e.g., conversations, eating, etc.). If treatment with DHIVY continues, advise patients not to drive and to avoid other potentially dangerous activities that might result in harm if the patients become somnolent. There is insufficient information to establish that dose reduction will eliminate episodes of falling asleep while engaged in activities of daily living.

5.2 Withdrawal-Emergent Hyperpyrexia and Confusion

A symptom complex that resembles neuroleptic malignant syndrome (characterized by elevated temperature, muscular rigidity, altered consciousness, and autonomic instability), with no other obvious etiology, has been reported in association with rapid dose reduction, withdrawal of, or changes in dopaminergic therapy. Avoid sudden discontinuation or rapid dose reduction in patients taking DHIVY. If the decision is made to discontinue DHIVY, the dose should be tapered to reduce the risk of hyperpyrexia and confusion [see Dosage and Administration (2.2)].

5.3 Cardiovascular Ischemic Events

In patients with a history of myocardial infarction who have residual atrial, nodal, or ventricular arrhythmias, cardiac function should be monitored in an intensive cardiac care facility during the period of initial dosage adjustment.

5.4 Hallucinations/Psychotic-Like Behavior

Hallucinations and psychotic-like behavior have been reported with dopaminergic medications. In general, hallucinations present shortly after the initiation of therapy and may be responsive to dose reduction in levodopa. Hallucinations may be accompanied by confusion, sleep disorder (insomnia), and excessive dreaming.

Abnormal thinking and behavior may present with one or more symptoms, including paranoid ideation, delusions, hallucinations, confusion, psychotic-like behavior, disorientation, aggressive behavior, agitation, and delirium.

Patients with a major psychotic disorder should not be treated with DHIVY, because of the risk of exacerbating psychosis. In addition, medications that antagonize the effects of dopamine used to treat psychosis may exacerbate the symptoms of Parkinson’s disease and may decrease the effectiveness of DHIVY [see Drug Interactions (7.2)].

5.5 Impulse Control/Compulsive Behaviors

Case reports suggest that patients can experience an intense urge to gamble, increased sexual urges, intense urges to spend money, binge eating, and/or other intense urges, and the inability to control these urges while taking one or more of the medications, including DHIVY, that increase central dopaminergic tone and that are generally used for the treatment of Parkinson’s disease. In some cases, although not all, these urges were reported to have stopped when the dosage was reduced or the medication was discontinued.

Because patients may not recognize these behaviors as abnormal, it is important for prescribers to specifically ask patients or the caregivers about the development of new or increased gambling urges, sexual urges, uncontrolled spending, or other urges while being treated with DHIVY.

Consider dosage reduction or stopping the medication if a patient develops such urges while taking DHIVY.

5.6 Dyskinesia

DHIVY can cause dyskinesias that may require a dosage reduction of DHIVY or other medications used for the treatment of Parkinson’s disease.

5.7 Peptic Ulcer Disease

Treatment with DHIVY may increase the possibility of upper gastrointestinal hemorrhage in patients with a history of peptic ulcer.

5.8 Glaucoma

DHIVY may cause increased intraocular pressure in patients with glaucoma. Monitor intraocular pressure in patients with glaucoma after starting DHIVY.

5.9 Laboratory Tests

DHIVY may cause a positive Coombs test or false-positive reaction for urinary ketone bodies when a test tape is used for determination of ketonuria. This reaction will not be altered by boiling the urine specimen. False-negative tests may result with the use of glucose-oxidase methods of testing for glucosuria.

Cases of falsely diagnosed pheochromocytoma in patients on carbidopa-levodopa therapy have been reported. Caution should be exercised when interpreting the plasma and urine levels of catecholamines and their metabolites in patients on carbidopa levodopa therapy.

5.10 Depression/Suicidality

All patients taking DHIVY should be observed carefully for the development of depression with concomitant suicidal tendencies.

6 ADVERSE REACTIONS

The following serious adverse reactions are discussed below and elsewhere in the labeling:

- Falling Asleep During Activities of Daily Living and Somnolence [see Warnings and Precautions (5.1)]
- Withdrawal-Emergent Hyperpyrexia and Confusion [see Warnings and Precautions (5.2)]
- Cardiovascular Ischemic Events [see Warnings and Precautions (5.3)]
- Hallucinations/Psychotic-Like Behavior [see Warnings and Precautions (5.4)]
- Impulse Control/Compulsive Behaviors [see Warnings and Precautions (5.5)]
- Dyskinesia [see Warnings and Precautions (5.6)]
- Peptic Ulcer Disease [see Warnings and Precautions (5.7)]
- Glaucoma [see Warnings and Precautions (5.8)]
- Depression//Suicidality [see Warnings and Precautions (5.10)]

The most common adverse reactions reported with carbidopa/levodopa tablets have included dyskinesias, such as choreiform, dystonic, and other involuntary movements, and nausea.

The following other adverse reactions have been reported with carbidopa/levodopa tablets:

Body as a Whole
Chest pain, asthenia.

Cardiovascular
Cardiac irregularities, hypotension, orthostatic effects including orthostatic hypotension, hypertension, syncope, phlebitis, palpitation.

Gastrointestinal
Dark saliva, gastrointestinal bleeding, development of duodenal ulcer, anorexia, vomiting, diarrhea, constipation, dyspepsia, dry mouth, taste alterations.

Hematologic
Agranulocytosis, hemolytic and non-hemolytic anemia, thrombocytopenia, leukopenia.

Hypersensitivity
Angioedema, urticaria, pruritus, Henoch-Schönlein purpura, bullous lesions (including pemphigus-like reactions).

Musculoskeletal
Back pain, shoulder pain, muscle cramps.

Nervous System/Psychiatric
Psychotic episodes including delusions, hallucinations, and paranoid ideation, bradykinetic episodes (“on-off” phenomenon), confusion, agitation, dizziness, somnolence, dream abnormalities including nightmares, insomnia, paresthesia, headache, depression with or without development of suicidal tendencies, dementia, pathological gambling, increased libido including hypersexuality, impulse control symptoms. Convulsions also have occurred; however, a causal relationship with DHIVY has not been established.

Respiratory
Dyspnea, upper respiratory infection.

Skin
Rash, increased sweating, alopecia, dark sweat.

Urogenital
Urinary tract infection, urinary frequency, dark urine.

Laboratory Tests
Decreased hemoglobin and hematocrit; abnormalities in alkaline phosphatase, SGOT (AST), SGPT (ALT), LDH, bilirubin, BUN, Coombs test; elevated serum glucose; white blood cells, bacteria, and blood in the urine.

Other adverse reactions that have been reported with levodopa alone and with various carbidopa levodopa formulations, and may occur with DHIVY are:

Body as a Whole
Abdominal pain and distress, fatigue.

Cardiovascular
Myocardial infarction.

Gastrointestinal
Gastrointestinal pain, dysphagia, sialorrhea, flatulence, bruxism, burning sensation of the tongue, heartburn, hiccups.

Metabolic
Edema, weight gain, weight loss.

Musculoskeletal
Leg pain.

Nervous System/Psychiatric
Ataxia, extrapyramidal disorder, falling, anxiety, gait abnormalities, nervousness, decreased mental acuity, memory impairment, disorientation, euphoria, blepharospasm (which may be taken as an early sign of excess dosage; consideration of dosage reduction may be made at this time), trismus, increased tremor, numbness, muscle twitching, activation of latent Horner’s syndrome, peripheral neuropathy.

Respiratory
Pharyngeal pain, cough.

Skin
Malignant melanoma, flushing.

Special Senses
Oculogyric crises, diplopia, blurred vision, dilated pupils.

Urogenital
Urinary retention, urinary incontinence, priapism.

Miscellaneous
Bizarre breathing patterns, faintness, hoarseness, malaise, hot flashes, sense of stimulation.

7 DRUG INTERACTIONS

7.1 Monoamine Oxidase (MAO) Inhibitors

The use of nonselective MAO inhibitors with DHIVY is contraindicated [see Contraindications (4)]. Discontinue use of any nonselective MAO inhibitors at least two weeks prior to initiating DHIVY.

DHIVY may be administered concomitantly with the manufacturer's recommended dose of selective MAO-B inhibitors (e.g., rasagiline or selegiline HCl). Concomitant therapy with selegiline and carbidopa/levodopa may be associated with severe orthostatic hypotension not attributable to carbidopa/levodopa alone.

7.2 Dopamine D2Receptor Antagonists and Isoniazid

Dopamine D2receptor antagonists (e.g., phenothiazines, butyrophenones, risperidone) and isoniazid may reduce the effectiveness of levodopa. Monitor patients taking these drugs with DHIVY for worsening Parkinson’s symptoms.

7.3 Iron Salts

Iron salts or multivitamins containing iron salts can form chelates with levodopa and carbidopa and can cause a reduction in the bioavailability of DHIVY. If iron salts or multivitamins containing iron salts are co-administered with DHIVY, monitor patients for worsening Parkinson’s symptoms.

7.4 Antihypertensive Drugs

Symptomatic postural hypotension occurred when carbidopa/levodopa was added to the treatment of a patient receiving antihypertensive drugs. Therefore, when therapy with DHIVY is started, dosage adjustment of the antihypertensive drug may be required.

7.5 Dopamine-Depleting Agents

Use of DHIVY with dopamine-depleting agents (e.g., reserpine and tetrabenazine) or other drugs known to deplete monoamine stores is not recommended.

7.6 Metoclopramide

Although metoclopramide may increase the bioavailability of levodopa by increasing gastric emptying, metoclopramide may also reduce effectiveness of levodopa by its dopamine receptor antagonistic properties.

8 USE IN SPECIFIC POPULATIONS

8.1 Pregnancy

Risk Summary

There are no adequate data on the developmental risk associated with the use of DHIVY in pregnant women. In animal studies, carbidopa/levodopa has been shown to be developmentally toxic (including teratogenic effects) at clinically relevant doses (see Data).

The estimated background risk of major birth defects and miscarriage in the indicated population is unknown. In the U.S. general population, the estimated background risk of major birth defects and miscarriage in clinically recognized pregnancies is 2% to 4% and 15% to 20%, respectively.

Data

Animal Data

When administered to pregnant rabbits throughout organogenesis, carbidopa-levodopa caused both visceral and skeletal malformations in fetuses at all doses and ratios of carbidopa-levodopa tested. No teratogenic effects were observed when carbidopa-levodopa was administered to pregnant mice throughout organogenesis.

8.2 Lactation

Risk Summary

Levodopa has been detected in human milk after administration of carbidopa-levodopa. There are no data on the presence of carbidopa in human milk, the effects of levodopa or carbidopa on the breastfed infant, or the effects on milk production. However, inhibition of lactation may occur because levodopa decreases secretion of prolactin in humans.

The developmental and health benefits of breastfeeding should be considered along with the mother’s clinical need for DHIVY and any potential adverse effects on the breastfed infant from DHIVY or from the underlying maternal condition.

8.4 Pediatric Use

Safety and effectiveness in pediatric patients have not been established.

8.5 Geriatric Use

Of the total number of subjects in clinical studies of immediate-release carbidopa-levodopa tablets (i.e., Sinemet®), almost half of the patients were older than age 65 years, and few were age 75 years and over. No overall differences in safety or effectiveness were observed between these subjects and younger subjects, but greater sensitivity of some older individuals to adverse drug reactions such as hallucinations cannot be ruled out.

The systemic exposure of levodopa was increased in elderly subjects compared to young subjects [see Clinical Pharmacology (12.3)]. There is no specific dosing recommendation based upon clinical pharmacology data as carbidopa/levodopa is titrated as tolerated for clinical effect.

10 OVERDOSAGE

Based on the limited available information, the acute symptoms of levodopa/dopa decarboxylase inhibitor overdosage can be expected to arise from dopaminergic overstimulation. Doses of a few grams may result in CNS disturbances, with an increasing likelihood of cardiovascular disturbance (e.g., hypotension, tachycardia) and more severe psychiatric problems at higher doses. An isolated report of rhabdomyolysis and another of transient renal insufficiency suggest that levodopa overdosage may give rise to systemic complications, secondary to dopaminergic overstimulation.

Monitor patients and provide supportive care. Patients should receive electrocardiographic monitoring for the development of arrhythmias; if needed, appropriate antiarrhythmic therapy should be given. The possibility that the patient may have taken other drugs, increasing the risk of drug interactions (especially catechol-structured drugs) should be taken into consideration.

11 DESCRIPTION

DHIVY®(carbidopa levodopa) is a combination of carbidopa, an inhibitor of aromatic amino acid decarboxylation, and levodopa, an aromatic amino acid, in tablets for oral use.

Carbidopa is a white, crystalline compound, slightly soluble in water, with a molecular weight of 244.3. It is designated chemically as (–)-L-α-hydrazino-α-methyl-β-(3,4-dihydroxy-benzene) propanoic acid monohydrate. It has a pKa of 2.3. Its molecular formula is C10H14N2O4•H2O and its structural formula is:

Tablet content is expressed in terms of anhydrous carbidopa, which has a molecular weight of 226.3.

Levodopa is a white, crystalline compound, slightly soluble in water, with a molecular weight of 197.2. It is designated chemically as (–)-L-α-amino-β-(3,4-dihydroxybenzene) propanoic acid. It has a pKa of 2.32. Its molecular formula is C9H11NO4and its structural formula is:

DHIVY is supplied as tablets for oral administration containing 25 mg of carbidopa and 100 mg of levodopa. The inactive ingredients are magnesium stearate, microcrystalline cellulose, and pregelatinized starch.

12 CLINICAL PHARMACOLOGY

12.1 Mechanism of Action

Carbidopa

When levodopa is administered orally, it is rapidly decarboxylated to dopamine in extracerebral tissues so that only a small portion of a given dose is transported unchanged to the central nervous system. Carbidopa inhibits the decarboxylation of peripheral levodopa, making more levodopa available for delivery to the brain.

Levodopa

Levodopa is the metabolic precursor of dopamine, does cross the blood-brain barrier, and presumably is converted to dopamine in the brain. This is thought to be the mechanism whereby levodopa treats symptoms of Parkinson’s disease.

12.2 Pharmacodynamics

Because its decarboxylase inhibiting activity is limited to extracerebral tissues, administration of carbidopa with levodopa makes more levodopa available to the brain. Carbidopa does not cross the blood-brain barrier and does not affect the metabolism of levodopa within the central nervous system. The addition of carbidopa to levodopa reduces the peripheral effects (nausea, vomiting) due to decarboxylation of levodopa; however, carbidopa does not decrease the adverse reactions due to the central effects of levodopa.

Patients treated with levodopa therapy for Parkinson's disease may develop motor fluctuations characterized by end-of-dose failure, peak dose dyskinesia, 'on-off' phenomenon, and akinesia.

12.3 Pharmacokinetics

Following single oral administration of a DHIVY tablet, DHIVY was shown to be bioequivalent to an immediate-release carbidopa/levodopa 25/100 mg tablet under fasting conditions for both carbidopa and levodopa.

Absorption

Following oral dosing of DHIVY under fasted conditions, the maximum concentration occurred at 3 hours for carbidopa and 1 hour for levodopa. The exposure of DHIVY after dose fractionation is proportional.

Effect of Food

In healthy adults, oral administration of DHIVY after a high-fat, high-calorie meal reduced levodopa Cmaxby approximately 25% while the AUC remained unchanged. The peak concentration of both carbidopa/levodopa were observed approximately 30 minutes later when DHIVY is taken with a high-fat, high-calorie meal.

Since levodopa competes with certain amino acids for transport across the gut wall, the absorption of levodopa may be impaired in some patients on a high protein diet [see Dosage and Administration (2.3)].

Distribution

Carbidopa is approximately 36% bound to plasma proteins. Levodopa is approximately 10% to 30% bound to plasma proteins.

Elimination

Following oral dosing of DHIVY under fasted conditions, the half-life was reported at approximately 3.5 hours for carbidopa and 2 hours for levodopa.

In clinical pharmacologic studies, simultaneous administration of carbidopa and levodopa produced greater urinary excretion of levodopa in proportion to the excretion of dopamine than administration of the two drugs at separate times.

Specific Populations

Geriatric Patients

A study in eight young healthy subjects (21-22 years) and eight elderly healthy subjects (69-76 years) showed that the absolute bioavailability of levodopa was similar between young and elderly subjects following oral administration of levodopa and carbidopa. However, the systemic exposure (AUC) of levodopa was increased by 55% in elderly subjects compared to young subjects. Based on another study in forty patients with Parkinson’s disease, there was a correlation between age of patients and the increase of AUC of levodopa following administration of levodopa and an inhibitor of peripheral dopa decarboxylase. AUC of levodopa was increased by 28% in elderly patients (≥ 65 years) compared to young patients (< 65 years). Additionally, mean value of Cmaxfor levodopa was increased by 24% in elderly patients (≥ 65 years) compared to young patients (< 65 years) [see Use in Specific Populations (8.5)].

The AUC of carbidopa was increased in elderly subjects (n=10, 65-76 years) by 29% compared to young subjects (n=24, 23-64 years) following IV administration of 50 mg levodopa with carbidopa (50 mg). This increase is not considered to have a clinically significant impact.

13 NONCLINICAL TOXICOLOGY

13.1 Carcinogenesis, Mutagenesis, Impairment of Fertility

Carcinogenesis

In rats, oral administration of carbidopa-levodopa for two years resulted in no evidence of carcinogenicity.

Impairment of Fertility

In reproduction studies, no effects on fertility were observed in rats receiving carbidopa-levodopa.

14 CLINICAL STUDIES

The efficacy of DHIVY is based upon bioavailability studies comparing DHIVY to an immediate-release tablet containing 25 mg of carbidopa and 100 mg of levodopa [see Clinical Pharmacology (12.3)].

16 HOW SUPPLIED/STORAGE AND HANDLING

16.1 How Supplied

DHIVY (carbidopa and levodopa) tablets are white to off-white tablets with functional scoring containing 25 mg of carbidopa and 100 mg of levodopa. One side of each DHIVY tablet has 3 scores, with each segment containing 6.25 mg of carbidopa and 25 mg of levodopa (1:4 ratio). The unscored side of the tablet is debossed with logo “AV70l”.

DHIVY is supplied as follows:

NDC75854-701-01 bottles of 100. Four copies of the Instructions for Use are included with the bottle, and additional copies, as needed, can be printed.

16.2 Storage and Handling

Store at 20°C to 25°C (68°F to 77°F); excursions permitted between 15°C to 30°C (59°F to 86°F) [see USP Controlled Room Temperature]. Store in a tightly closed container, protected from light and moisture.

Dispense in a light-resistant container.

17 PATIENT COUNSELING INFORMATION

Dosing Instructions

- It is important that DHIVY be taken at regular intervals according to the schedule outlined by their physician. Inform the patient not to change the prescribed dosage regimen and not to add any additional antiparkinson medications, including other carbidopa-levodopa preparations, without first consulting their physician. Advise patients to call their healthcare provider before stopping DHIVY. Discontinue DHIVY slowly. Tell patients to call their healthcare provider if they develop withdrawal symptoms such as fever and confusion [see Dosage and Administration (2.2)and Warnings and Precautions (5.2)] .
- Advise patients to swallow DHIVY with or without food. If the patient has difficulty swallowing the tablet due to its size, inform the patient that the tablet can be broken at the score lines [see Dosage and Administration (2.3)] .
- Advise the patient that occasionally, dark color (red, brown, or black) may appear in saliva, urine, or sweat after ingestion of DHIVY. Although the color appears to be clinically insignificant, garments may become discolored.
- Advise the patient that a change in diet to foods that are high in protein or taking iron salts or multivitamins with iron may delay the absorption of levodopa and may reduce the amount taken up in the circulation. Excessive acidity also delays stomach emptying, thus delaying the absorption of levodopa.

Falling Asleep

Advise patients that certain side effects such as sleepiness and dizziness that have been reported with DHIVY may affect some patients’ ability to drive and operate machinery safely [see Warnings and Precautions (5.1) and Adverse Reactions (6)].

Hallucinations and Psychosis

Inform patients that hallucinations can occur with levodopa products [see Warnings and Precautions (5.4)].

Impulse Control Disorder

Inform patients of the potential for experiencing intense urges to gamble, increased sexual urges, and other intense urges and the inability to control these urges while taking one or more of the medications that increase central dopaminergic tone, that are generally used for the treatment of Parkinson’s disease [see Warnings and Precautions (5.5)].

Dyskinesia

Instruct patients to notify their healthcare provider if abnormal involuntary movements appear or get worse during treatment with DHIVY [see Warnings and Precautions (5.6)].

Pregnancy and Breastfeeding

Advise patients to notify their healthcare provider if they become pregnant or intend to become pregnant during DHIVY therapy [see Use in Specific Populations (8.1)].

Advise female patients to notify their physicians if they intend to breastfeed or are breastfeeding an infant [see Use in Specific Populations (8.2)].

Distributed by:
Avion Pharmaceuticals, LLC
Alpharetta, GA, 30005 USA

L-0344 Rev. 0423-02

INSTRUCTIONS FOR USE

DHIVY (DHI-VEE)

(carbidopa and levodopa)

tablets, for oral use

This Instructions for Use contains information on how to take DHIVY.

Important Information You Need to Know Before Taking DHIVY

- Take DHIVY exactly as your healthcare provider tells you to take it. Your healthcare provider may increase your dose every day or every other day as needed until you reach the recommended dosage.
- Take DHIVY by mouth, with or without food.
- 1 whole DHIVY tablet contains 25 mg of carbidopa and 100 mg of levodopa.
- 1 DHIVY tablet has 3 grooves (score lines) that can be split into 4 segments so that you can take your prescribed dose. (See the DHIVY tablet image below.)
- If you have trouble swallowing the DHIVY tablet, you can break the tablet at the groove (score lines). Then take the number of segments that equal your prescribed dose. Each segment of 1 DHIVY tablet contains 6.25 mg of carbidopa and 25 mg of levodopa. (See Table 1 below to help determine how many tablet segments to take.)
- Do not change your dose or take any additional antiparkinson medicines (including medicines that contain carbidopa and levodopa) without first talking to your healthcare provider. If you are not sure if you take these medicines, ask your healthcare provider.
- Call your healthcare provider before you stop taking DHIVY. Call your healthcare provider if you develop withdrawal symptoms such as fever and confusion.
- Changing your diet to highly acidic foods or foods that are high in protein or taking iron salts or multivitamins with iron may affect how DHIVY works. If you are not sure if you are on any of these diets or taking any of these medicines, ask your healthcare provider.

DHIVY Tablet

Dhivy tablet has four segments. Each segment contains 6.25 mg of carbidopa and 25 mg of levodopa. The top layer of the tablet (above the dotted line) contains the carbidopa and levodopa. The bottom layer of the tablet (below the dotted line) contains the inactive ingredients.

Table 1: DHIVY Segment Description

Number of DHIVY Segments | Image of number of Dhivy segments | Strength of Carbidopa/Levodopa
1 |  | 6.25 mg / 25 mg
2 |  | 12.5 mg / 50 mg
3 |  | 18.75 mg / 75 mg
4 (whole tablet) |  | 25 mg / 100 mg

How to take 3 Segments (18.75 mg of carbidopa and 75 mg of levodopa)

- Hold the DHIVY tablet with 1 hand on each side.
- Carefully grasp 1 segment on either side and break the tablet at the groove to get 3 segments containing 18.75 mg of carbidopa and 75 mg of levodopa and 1 segment containing 6.25 mg of carbidopa and 25 mg of levodopa.
- Put the remaining 1 segment back into the container and close tightly.

How to take 2 Segments (12.5 mg of carbidopa and 50 mg of levodopa)

- Hold the DHIVY tablet with 1 hand on each side.
- Carefully grasp 2 segments and break the tablet in half at the groove in the middle to get 2 segments containing 12.5 mg of carbidopa and 50 mg of levodopa each.
- Put the remaining 2 segments back into the container and close tightly.

How to take 1 Segment (6.25 mg of carbidopa and 25 mg of levodopa)

- Hold the DHIVY tablet with 1 hand on each side.
- Carefully grasp 1 segment on either side and break the tablet at the groove to get 1 segment containing 6.25 mg of carbidopa and 25 mg of levodopa and 3 segments containing 18.75 mg of carbidopa and 75 mg of levodopa.
- Put the remaining 3 segments back into the container and close tightly.

Storing DHIVY

- Store DHIVY at room temperature between 68°F to 77°F (20°C to 25°C).
- Store DHIVY in a tightly closed container to protect it from light and moisture.
- Keep DHIVY and all medicines out of the reach of children.

To report side effects, call Avion Pharmaceuticals at 888-612-8466 or FDA at 1-800-FDA-1088 or www.fda.gov/medwatch.

Distributed by:

Avion Pharmaceuticals, LLC

Alpharetta, GA, 30005 USA

1-888-612-8466

This Instructions for Use has been approved by the U.S. Food and Drug Administration.

Approved: 06/2022